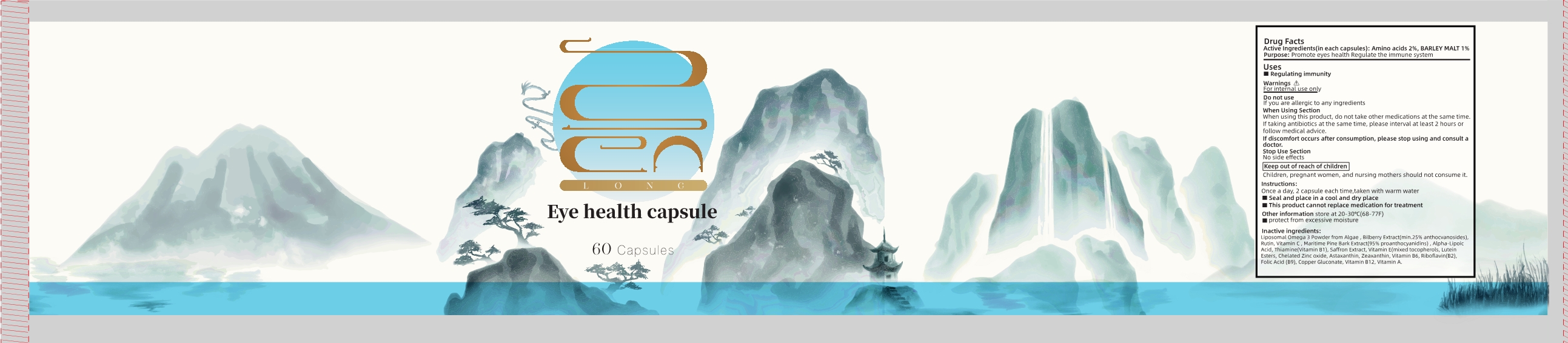 DRUG LABEL: Eye health
NDC: 83739-006 | Form: CAPSULE
Manufacturer: XIAN CHIANG COMPANY LIMITED
Category: otc | Type: HUMAN OTC DRUG LABEL
Date: 20250216

ACTIVE INGREDIENTS: BARLEY MALT 1 g/100 1; AMINO ACIDS 2 g/100 1
INACTIVE INGREDIENTS: OMEGA-3 FATTY ACIDS; RUTIN; MARITIME PINE; .ALPHA.-LIPOIC ACID; CROCUS SATIVUS FLOWER; .ALPHA.-TOCOPHEROL; PYRIDOXINE; VITAMIN A; LUTEIN; ZINC OXIDE; ASTAXANTHIN; RIBOFLAVIN; COPPER GLUCONATE; ZEAXANTHIN; CYANOCOBALAMIN; ASCORBIC ACID; THIAMINE; FOLIC ACID; VACCINIUM MYRTILLUS ANTHOCYANOSIDES

83739-006

ACTIVE INGREDIENT

Amino acids 2%,BARLEY MALT 1%

Purpose

Promote eyes health Regulate the immune system

Uses

Regulating immunity

Warnings

For internal use only

Do not use

If you are allergic to any ingredients

When Using Section

When using this product , do not take other medications at the same timeIf taking antibiotics at the same time ,If taking antibiotics at the same time , please interval at least 2 hours or follow medical advice

If discomfort occurs after consumption , please stop using and consult a doctor

Stop Use Section

No side effects

keep out of reach of children

Children , pregnant women , and nursing mothers should not consume

Instructions

Once a day , 2 capsule each time , taken with warm water

Seal and place in a cool and dry place

This product cannot replace medication for treatment

Other information store at 20-30°C (68-77F)

protect from excessive moisture

Inactive ingredients

Liposomal Omega 3 Powder from Algae , Bilberry Extract (min . 25% anthocvanosides), Rutin , Vitamin C , Maritime Pine Bark Extract (95 % proanthocyanidins) , Alpha-lipoic Acid , Thiamine (Vitamin B1) , Saffron Extract , Vitamin E (mixed tocopherols , Lutein Esters , Chelated Zinc oxide , Astaxanthin , Zeaxanthin , Vitamin B6 , Riboflavin (B2) ,Folic Acid (B9) , Copper Gluconate , Vitamin B12 , Vitamin A